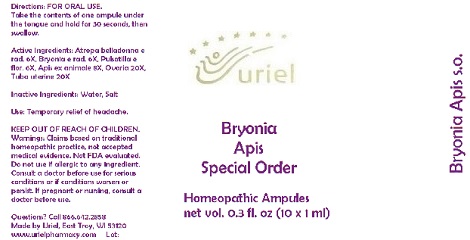 DRUG LABEL: Bryonia Apis Special Order
NDC: 48951-2082 | Form: LIQUID
Manufacturer: Uriel Pharmacy Inc.
Category: homeopathic | Type: HUMAN OTC DRUG LABEL
Date: 20170731

ACTIVE INGREDIENTS: ATROPA BELLADONNA 6 [hp_X]/1 mL; BRYONIA ALBA ROOT 6 [hp_X]/1 mL; PULSATILLA VULGARIS 6 [hp_X]/1 mL; APIS MELLIFERA 8 [hp_X]/1 mL; BOS TAURUS OVARY 20 [hp_X]/1 mL; SUS SCROFA FALLOPIAN TUBE 20 [hp_X]/1 mL
INACTIVE INGREDIENTS: WATER; SODIUM CHLORIDE

Bryonia Apis Special Order

INDICATIONS AND USAGE

Directions: FOR ORAL USE.

DOSAGE AND ADMINISTRATION

Take the contents of one ampule under the tongue and hold for 30 seconds, then swallow.

ACTIVE INGREDIENT

Active Ingredients: Atropa belladonna e rad. 6X, Bryonia e rad. 6X, Pulsatilla e flor. 6X, Apis ex animale 8X, Ovaria 20X, Tuba uterine 20X

Inactive Ingredients: Water, Salt

PURPOSE

Use: Temporary relief of headache.

KEEP OUT OF REACH OF CHILDREN.

WARNINGS

Warnings: Claims based on traditional homeopathic practice, not accepted medical evidence. Not FDA evaluated. Do not use if allergic to any ingredient. Consult a doctor before use for serious conditions or if conditions worsen or persist. If pregnant or nursing, consult a doctor before use.

QUESTIONS

Questions? Call 866.642.2858 Made by Uriel, East Troy, WI 53120 www.urielpharmacy.com